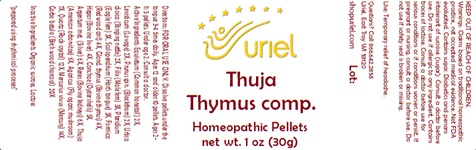 DRUG LABEL: Thuja Thymus comp.
NDC: 48951-9362 | Form: PELLET
Manufacturer: Uriel Pharmacy Inc.
Category: homeopathic | Type: HUMAN OTC DRUG LABEL
Date: 20240115

ACTIVE INGREDIENTS: SLOE 2 [hp_X]/1 1; DRYOPTERIS FILIX-MAS ROOT 3 [hp_X]/1 1; PTERIDIUM AQUILINUM WHOLE 3 [hp_X]/1 1; URTICA DIOICA 2 [hp_X]/1 1; BOS TAURUS THYMUS 4 [hp_X]/1 1; BEEF LIVER 4 [hp_X]/1 1; THUJA OCCIDENTALIS WHOLE 6 [hp_X]/1 1; PORK KIDNEY 6 [hp_X]/1 1; ASPLENIUM SCOLOPENDRIUM TOP 3 [hp_X]/1 1; OSTREA EDULIS SHELL 5 [hp_X]/1 1; SILVER 6 [hp_X]/1 1; SILICON DIOXIDE 12 [hp_X]/1 1; MERCURY 14 [hp_X]/1 1; ACTIVATED CHARCOAL 20 [hp_X]/1 1; FORMICA RUFA 4 [hp_X]/1 1; AMANITA MUSCARIA FRUITING BODY 7 [hp_X]/1 1; EQUISETUM ARVENSE TOP 2 [hp_X]/1 1; LEVISTICUM OFFICINALE ROOT 2 [hp_X]/1 1
INACTIVE INGREDIENTS: SUCROSE; LACTOSE, UNSPECIFIED FORM

Thuja Thymus comp.

INDICATIONS AND USAGE

Directions: FOR ORAL USE ONLY.

DOSAGE AND ADMINISTRATION

Dissolve pellets under the tongue 3-4 times daily. Ages 12 and older: 10 pellets. Ages 2-11: 5 pellets. Under age 2: Consult a doctor.

ACTIVE INGREDIENT

Active Ingredients: Equisetum (Common horsetail) 2X, Levisticum (Lovage) 2X, Prunus spin. (Blackthorn) 2X, Urtica dioica (Stinging nettle) 2X, Filix (Male fern) 3X, Pteridium (Eagle fern) 3X, Scolopendrium (Hart's tongue) 3X, Formica (Red wood ant) 4X, Gland. thymus (Bovine thymus) 4X, Hepar (Bovine liver) 4X, Conchae (Oyster shells) 5X, Argentum met. (Silver) 6X, Renes (Bovine kidneys) 6X, Thuja (American arborvitae) 6X, Agaricus (Fly agaric mushroom) 7X, Quartz (Rock crystal) 12X, Mercurius vivus (Mercury) 14X, Carbo betula (Birch wood charcoal) 20X

Inactive Ingredients: Organic sucrose, Lactose

"prepared using rhythmical processes"

PURPOSE

Use: Temporary relief of headache.

KEEP OUT OF REACH OF CHILDREN.

WARNINGS

Warnings: Claims based on traditional homeopathic practice, not accepted medical evidence. Not FDA evaluated. Contains sugar. Diabetics and persons intolerant of sucrose (sugar): Consult a doctor before use.Do not use if allergic to any ingredient. Contains traces of lactose. Consult a doctor before use for serious conditions or if conditions worsen or persist. If pregnant or nursing, consult a doctor before use. Do not use if safety seal is broken or missing.

Questions? Call 866.642.2858
Uriel, East Troy, WI 53120
shopuriel.com Lot: